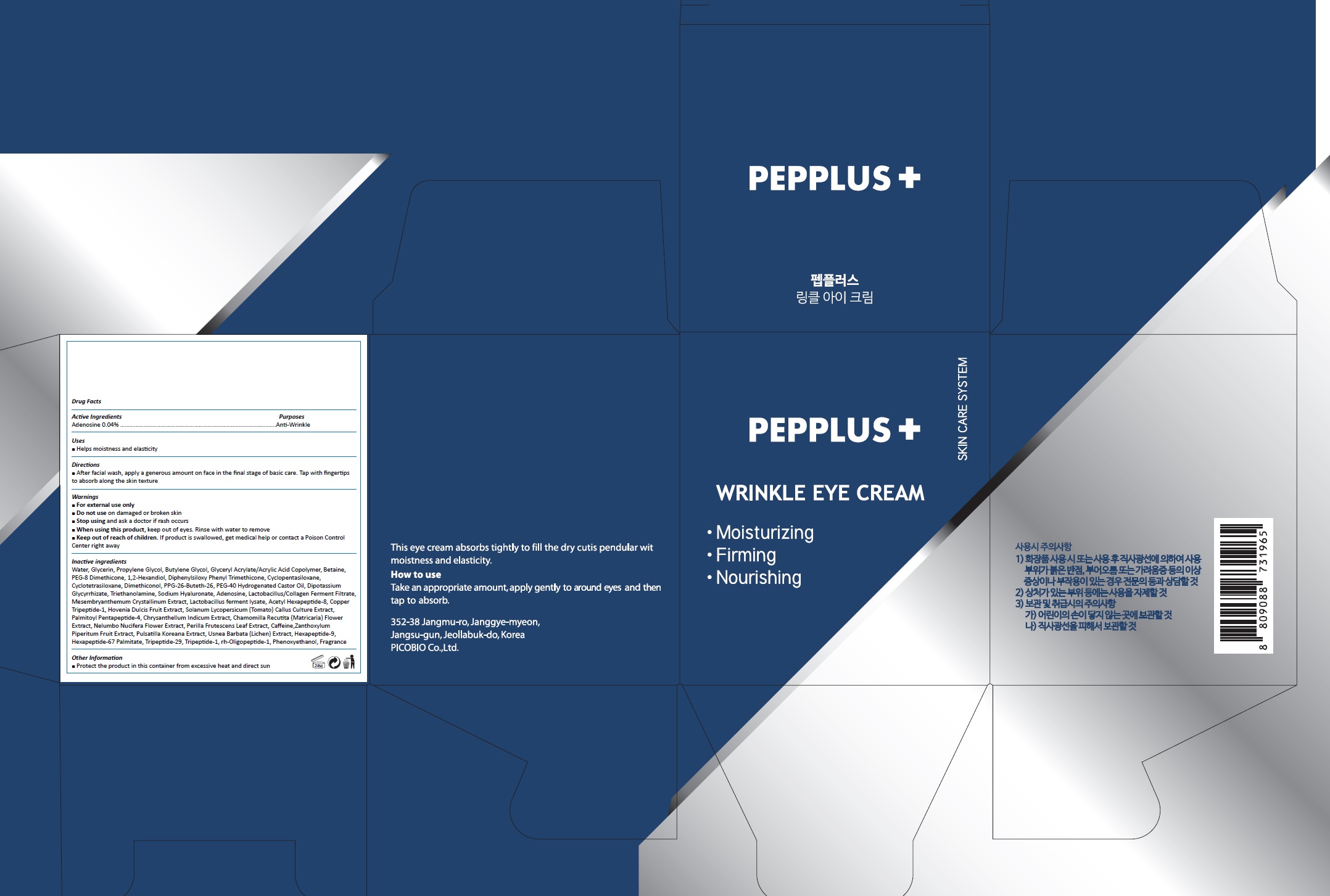 DRUG LABEL: PEPPLUS WRINKLE EYE
NDC: 72211-004 | Form: CREAM
Manufacturer: Picobio Co., Ltd
Category: otc | Type: HUMAN OTC DRUG LABEL
Date: 20211102

ACTIVE INGREDIENTS: ADENOSINE 0.012 g/30 g
INACTIVE INGREDIENTS: WATER; GLYCERIN; PROPYLENE GLYCOL; BUTYLENE GLYCOL; BETAINE; PEG-8 DIMETHICONE

72211-004

ACTIVE INGREDIENT

Adenosine 0.04%

PURPOSE

Anti-wrinkle

INDICATIONS AND USAGE

Helps moistness and elasticity

DOSAGE AND ADMINISTRATION

After facial wash, apply a generous amount on face in the final stage of basic care. Tap with fingertips to absorb along the skin texture

WARNINGS

For external use only.
Do not use on damaged or broken skin.
When using this product, keep out of eyes. Rinse with water to remove.
Stop using and ask a doctor if rash occurs.

KEEP OUT OF REACH OF CHILDREN

Keep out of reach of the children. If product is swallowed, get medical help or contact a poison control center right away.

INACTIVE INGREDIENT

Water, Glycerin, Propylene Glycol, Butylene Glycol, Glyceryl Acrylate/Acrylic Acid Copolymer, Betaine, PEG-8 Dimethicone, Sodium Hyaluronate, Nelumbo Nucifera Flower Extract, Chrysanthellum Indicum Extract, Chamomilla Recutita (Matricaris) Flower Extract, Lactobacillus ferment lysate, Perilla Frutescens Leaf Extract, Mesembryanthemum Crystallinum Extract, Lactobacillus/Collagen Ferment Filtrate, Solanum Lycopersicum (Tomato) Fruit/Leaf/Stem Extract, Hovenia Dulcis Fruit Extract, Caffeine, Phenyl Trimethicone, Phenoxyethanol, Polysorbate 20, Cyclopentasiloxane, Cyclotetrasiloxane, Dimethiconol, PPG-26-Buteth-26, PEG-40 Hydrogenated Castor Oil, Dipotassium Glycyrrhizate, Triethanolamine, 1,2-Hexanediol, Copper Tripeptide-1, Acetyl Hexapeptide-8, Palmitoyl Pentapeptide-4, Hexapeptide-9, Tripeptide-29, Tripeptide-1, Hexapeptide-67 Palmitate, rh-Oligopeptide-1, Perfume